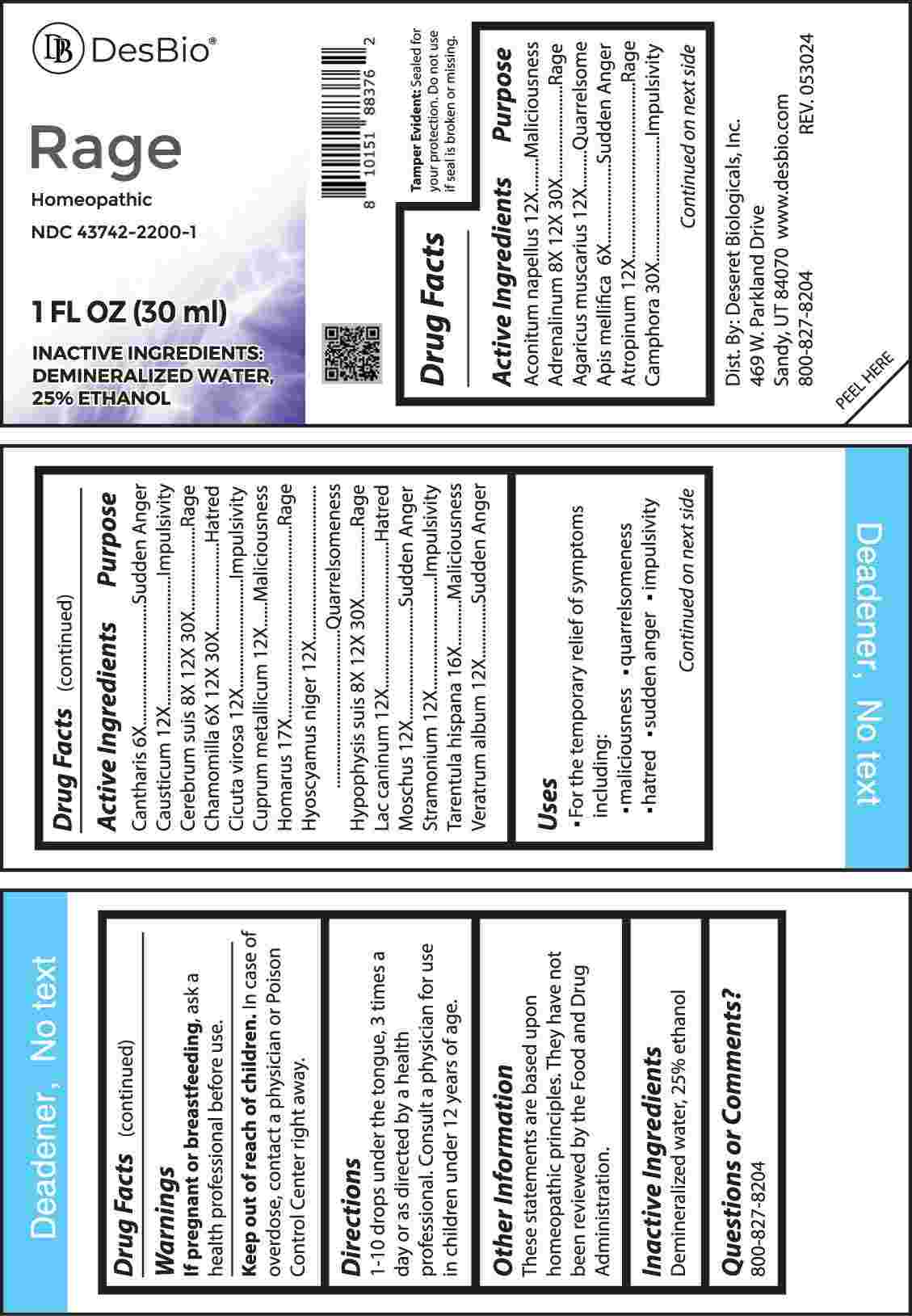 DRUG LABEL: Rage
NDC: 43742-2200 | Form: LIQUID
Manufacturer: Deseret Biologicals, Inc.
Category: homeopathic | Type: HUMAN OTC DRUG LABEL
Date: 20241106

ACTIVE INGREDIENTS: ACONITUM NAPELLUS WHOLE 12 [hp_X]/1 mL; EPINEPHRINE 8 [hp_X]/1 mL; AMANITA MUSCARIA FRUITING BODY 12 [hp_X]/1 mL; APIS MELLIFERA 6 [hp_X]/1 mL; ATROPINE 12 [hp_X]/1 mL; CAMPHOR (NATURAL) 30 [hp_X]/1 mL; LYTTA VESICATORIA 6 [hp_X]/1 mL; CAUSTICUM 12 [hp_X]/1 mL; SUS SCROFA CEREBRUM 8 [hp_X]/1 mL; MATRICARIA CHAMOMILLA WHOLE 6 [hp_X]/1 mL; CICUTA VIROSA ROOT 12 [hp_X]/1 mL; COPPER 12 [hp_X]/1 mL; HOMARUS AMERICANUS DIGESTIVE FLUID 17 [hp_X]/1 mL; HYOSCYAMUS NIGER 12 [hp_X]/1 mL; SUS SCROFA PITUITARY GLAND 8 [hp_X]/1 mL; CANIS LUPUS FAMILIARIS MILK 12 [hp_X]/1 mL; MOSCHUS MOSCHIFERUS MUSK SAC RESIN 12 [hp_X]/1 mL; DATURA STRAMONIUM 12 [hp_X]/1 mL; LYCOSA TARANTULA 16 [hp_X]/1 mL; VERATRUM ALBUM ROOT 12 [hp_X]/1 mL
INACTIVE INGREDIENTS: WATER; ALCOHOL

DRUG FACTS:

ACTIVE INGREDIENTS:

Aconitum Napellus, Adrenalinum, Agaricus Muscarius, Apis Mellifica, Atropinum, Camphora, Cantharis, Causticum, Cerebrum Suis, Chamomilla, Cicuta Virosa, Cuprum Metallicum, Homarus, Hyoscyamus Niger, Hypophysis Suis, Lac Caninum, Moschus, Stramonium, Tarentula Hispana, Veratrum Album

PURPOSE:

Aconitum Napellus - Maliciousness, Adrenalinum - Rage, Agaricus Muscarius - Quarrelsome, Apis Mellifica – Sudden Anger, Atropinum - Rage, Camphora - Impulsivity, Cantharis – Sudden Anger, Causticum - Impulsivity, Cerebrum Suis - Rage, Chamomilla - Hatred, Cicuta Virosa - Impulsivity, Cuprum Metallicum - Maliciousness, Homarus - Rage, Hyoscyamus Niger - Quarrelsomeness, Hypophysis Suis - Rage, Lac Caninum - Hatred, Moschus – Sudden Anger, Stramonium - Impulsivity, Tarentula Hispana - Maliciousness, Veratrum Album – Sudden Anger

USES:

• For the temporary relief of symptoms including:

• maliciousness • quarrelsomeness • hatred • sudden anger • impulsivity

These statements are based upon homeopathic principles. They have not been reviewed by the Food and Drug Administration.

WARNINGS:

If pregnant or breast-feeding, ask a health professional before use.

Keep out of reach of children. In case of overdose, contact a physician or Poison Control Center right away.

Tamper Evident: Sealed for your protection. Do not use if seal is broken or missing.

KEEP OUT OF REACH OF CHILDREN:

In case of overdose, contact a physician or Poison Control Center right away.

DIRECTIONS:

1-10 drops under the tongue, 3 times a day or as directed by a health professional. Consult a physician for use in children under 12 years of age.

INACTIVE INGREDIENTS:

Demineralized water, 25% ethanol

QUESTIONS:

Dist. By: Deseret Biologicals, Inc.

469 W. Parkland Drive

Sandy, UT 84070

www.desbio.com

800-827-8204

PACKAGE LABEL DISPLAY:

DesBio

Rage

Homeopathic

NDC 43742-2200-1

1Fl OZ (30 ml)